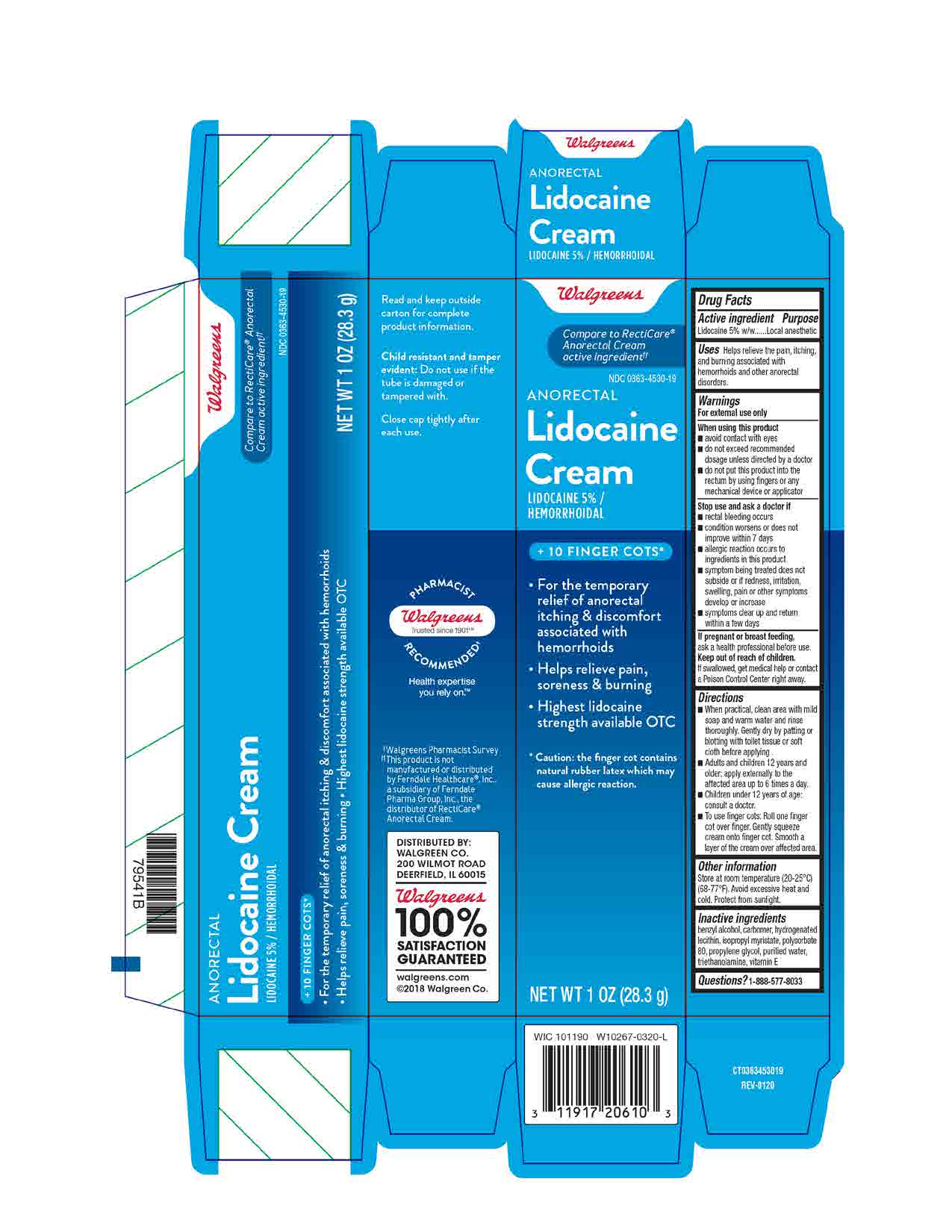 DRUG LABEL: Lidocaine 5%
NDC: 0363-4530 | Form: OINTMENT
Manufacturer: WALGREENS CO.
Category: otc | Type: HUMAN OTC DRUG LABEL
Date: 20201015

ACTIVE INGREDIENTS: LIDOCAINE 5 g/100 g
INACTIVE INGREDIENTS: HYDROGENATED SOYBEAN LECITHIN; WATER; BENZYL ALCOHOL; CARBOMER 940; ISOPROPYL MYRISTATE; POLYSORBATE 80; PROPYLENE GLYCOL; TROLAMINE; .ALPHA.-TOCOPHEROL ACETATE

Walgreens Anorectal Lidocaine Cream
Lidocaine 5%

ACTIVE INGREDIENT

Lidocaine HCl 5%

INACTIVE INGREDIENT

benzyl alcohol, carbomer, hydrogenated lecithin, isopropyl myristate, polysorbate 80, propylene glycol, triethanolamine, vitamin E, purified water.

DOSAGE AND ADMINISTRATION

When practical, clean area with mild soap and warm water and rinse thoroughly. Gently dry by patting or blotting with toilet tissue or soft cloth before applying.

Adults and children 12 years and older: apply externally to the affected area up to 6 times a day.

Children under 12 years: consult a doctor

To use finger cots: Roll one finger cot over finger. Gently squeeze cream over affected area.

INDICATIONS AND USAGE

helps relieve the pain, itching, and burning associated with hemorrhoids and other anorectal disorders.

WARNINGS

For external use only

When using this product avoid contact with eyes, do not exceed recommended dosage unless directed by a doctor, do not put this product into the rectum by using fingers or any mechanical device or applicator.

Stop use and ask a doctor if rectal bleeding occurs, condition worsens or does not improve within 7 days, allergic reaction occurs to ingredients in this product, symptom being treated does not subside or if redness, irritation, swelling, pain, or other symptoms develop or increase, symptoms clear up and return within a few days.

If pregnant or breast-feeding, ask a health professional before use.

Keep out of reach of children.

If swallowed, get medical help or contact a Poison Control Center right away.

Keep out of reach of children.

If swallowed, get medical help or contact a Poison Control Center right away.

PURPOSE

Local anesthetic

OTHER SAFETY INFORMATION

Store at room temperature (20-25 C) (68-77 F). Avoid excessive heat and cold. Protect from sunlight.